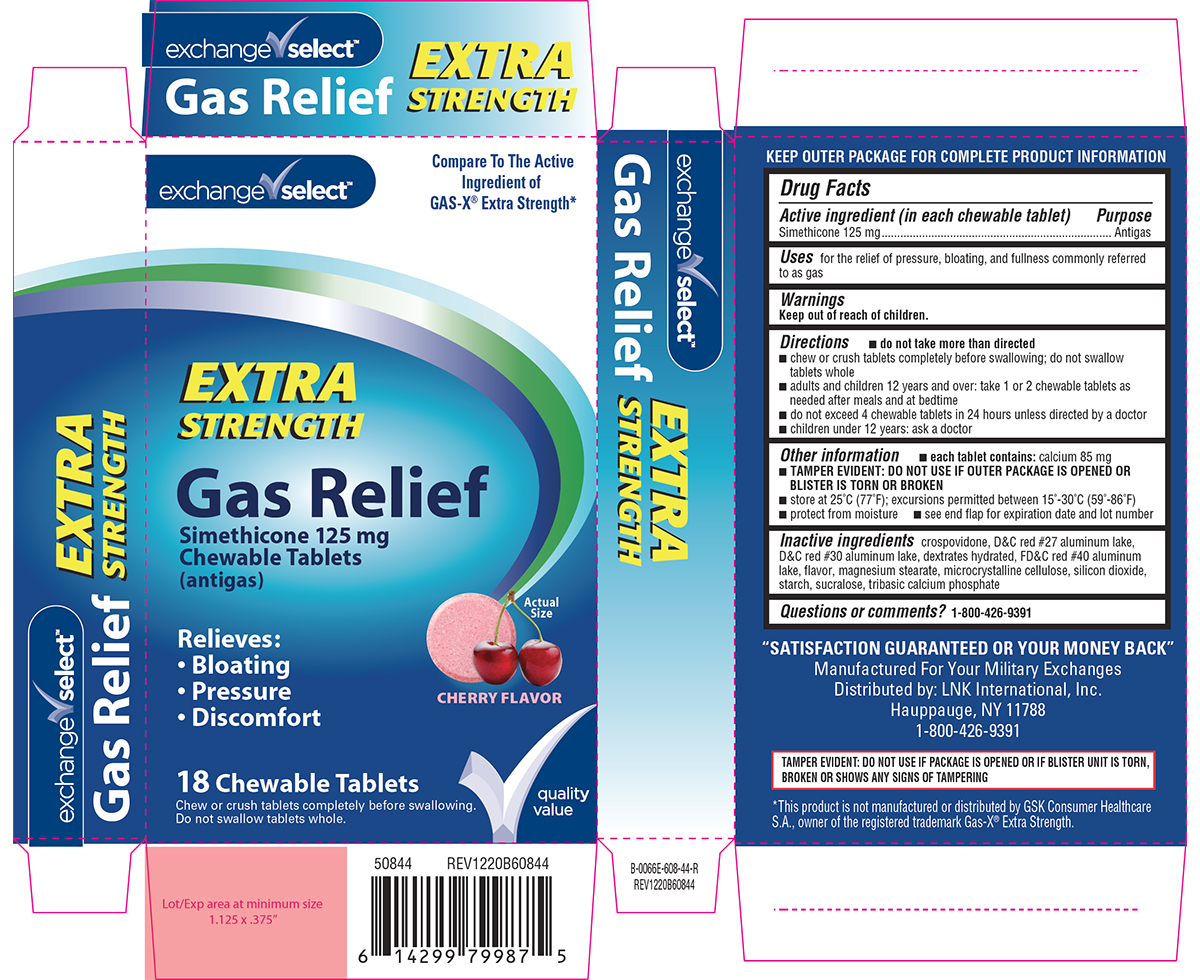 DRUG LABEL: Gas Relief
NDC: 55301-680 | Form: TABLET, CHEWABLE
Manufacturer: ARMY AND AIR FORCE EXCHANGE SERVICE
Category: otc | Type: HUMAN OTC DRUG LABEL
Date: 20250929

ACTIVE INGREDIENTS: DIMETHICONE 125 mg/1 1
INACTIVE INGREDIENTS: CROSPOVIDONE, UNSPECIFIED; D&C RED NO. 27 ALUMINUM LAKE; D&C RED NO. 30 ALUMINUM LAKE; DEXTROSE MONOHYDRATE; FD&C RED NO. 40 ALUMINUM LAKE; MAGNESIUM STEARATE; MICROCRYSTALLINE CELLULOSE; SILICON DIOXIDE; STARCH, CORN; SUCRALOSE; TRIBASIC CALCIUM PHOSPHATE; DIMETHICONE 410

Exchange Select 44-608

Active ingredient (in each chewable tablet)

Simethicone 125 mg

Purpose

Antigas

Uses

for the relief of pressure, bloating, and fullness commonly referred to as gas

Directions

- do not take more than directed
- chew or crush tablets completely before swallowing; do not swallow tablets whole
- adults and children 12 years and over: take 1 or 2 chewable tablets as needed after meals and at bedtime
- do not exceed 4 chewable tablets in 24 hours unless directed by a doctor
- children under 12 years: ask a doctor

Other information

- each tablet contains: calcium 85 mg
- TAMPER EVIDENT: DO NOT USE IF OUTER PACKAGE IS OPENED OR BLISTER IS TORN OR BROKEN
- store at 25ºC (77ºF); excursions permitted between 15º-30ºC (59º-86ºF)
- protect from moisture
- see end flap for expiration date and lot number

Inactive ingredients

crospovidone, D&C red #27 aluminum lake, D&C red #30 aluminum lake, dextrates hydrated, FD&C red #40 aluminum lake, flavor, magnesium stearate, microcrystalline cellulose, silicon dioxide, starch, sucralose, tribasic calcium phosphate

Questions or comments?

1-800-426-9391

Principal display panel

exchange✓select™

Compare To The Active
Ingredient of
GAS-X® Extra Strength*

EXTRA
STRENGTH

Gas Relief
Simethicone 125 mg
Chewable Tablets
(antigas)

Relieves:
• Bloating
• Pressure
• Discomfort

CHERRY
FLAVOR

Actual
Size

18 Chewable Tablets

Chew or crush tablets completely before swallowing.
Do not swallow tablets whole.

✓quality
value

TAMPER EVIDENT: DO NOT USE IF PACKAGE IS OPENED OR IF BLISTER UNIT IS TORN,
BROKEN OR SHOWS ANY SIGNS OF TAMPERING

*This product is not manufactured or distributed by GSK Consumer Healthcare
S.A., owner of the registered trademark Gas-X® Extra Strength.

"SATISFACTION GUARANTEED OR YOUR MONEY BACK"
Manufactured For Your Military Exchanges
Distributed by: LNK International, Inc.
Hauppauge, NY 11788
1-800-426-9391

50844 REV1220B60844

Exchange Select 44-608